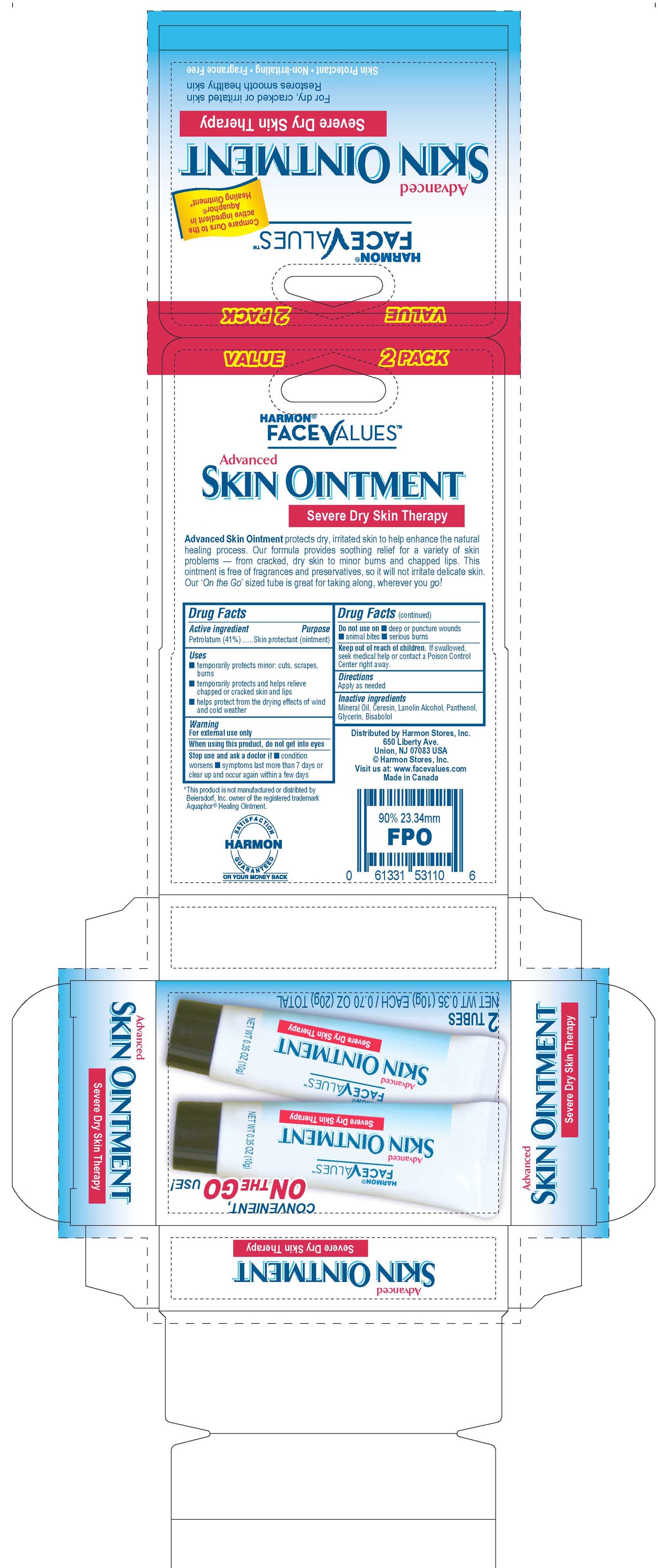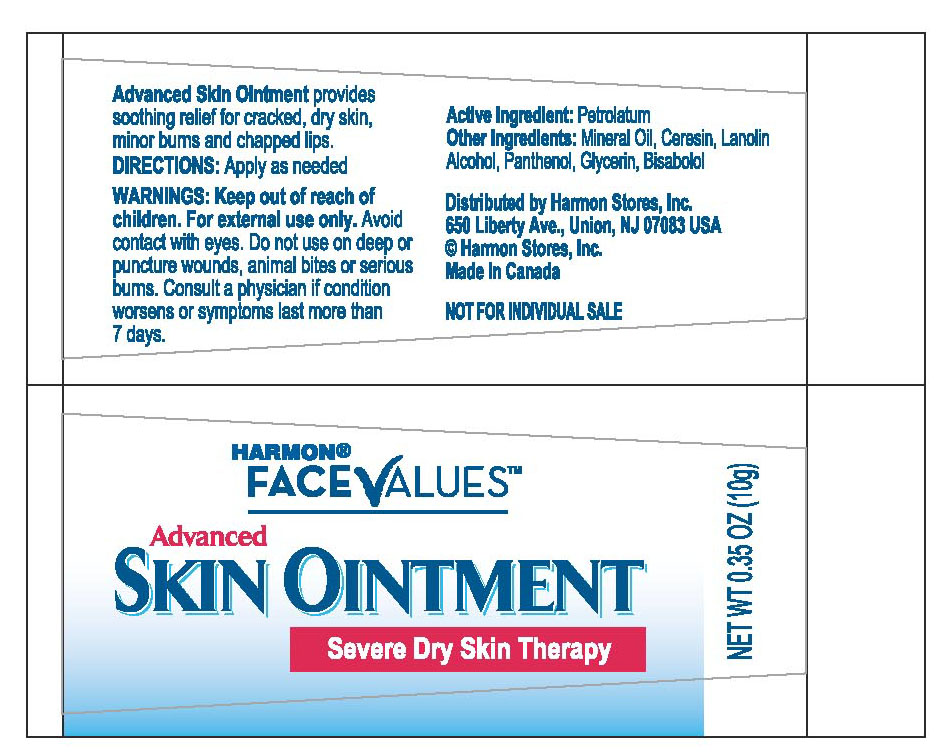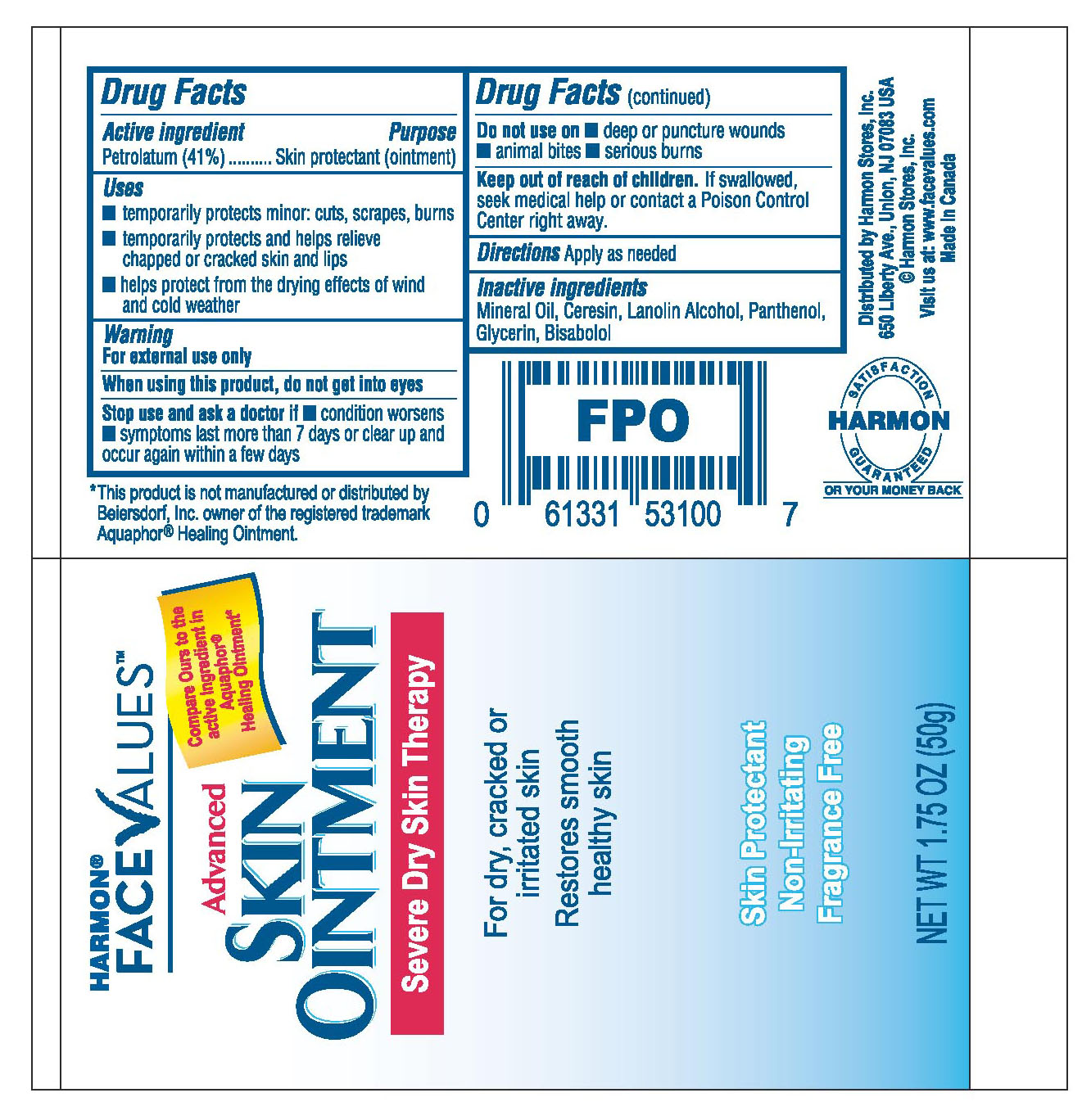 DRUG LABEL: Harmon Face Values Advanced 
NDC: 66353-100 | Form: OINTMENT
Manufacturer: Delta Pharma Inc.
Category: otc | Type: HUMAN OTC DRUG LABEL
Date: 20181212

ACTIVE INGREDIENTS: Petrolatum 41 g/100 g
INACTIVE INGREDIENTS: Mineral Oil; Ceresin; LANOLIN ALCOHOLS; Panthenol; Glycerin; LEVOMENOL

Harmon Face Values Advanced Skin Ointment

Active Ingredient

Petrolatum (41%)

Purpose

Skin Protectant (ointment)

Uses

- temporarily protects minor: cuts, scrapes, burns
- temporarily protects and helps relieve chapped or cracked skin and lips
- helps protect from the drying effects of wind and cold weather

Warning
For external use only

When using this product, do not get into eyes

Stop use and ask a doctor if

- condition worsens
- symptoms last more than 7 days or clear up and occur again within a few days

Do not use on

- deep or puncture wounds
- animal bites
- serious burns

Keep out of the reach of children.

If swallowed, seek medical help or contact a Poison Control Center right away.

Directions

Apply as needed

Inactive Ingredients

Mineral Oil, Ceresin, Lanolin Alcohol, Panthenol, Glycerin, Bisabolol